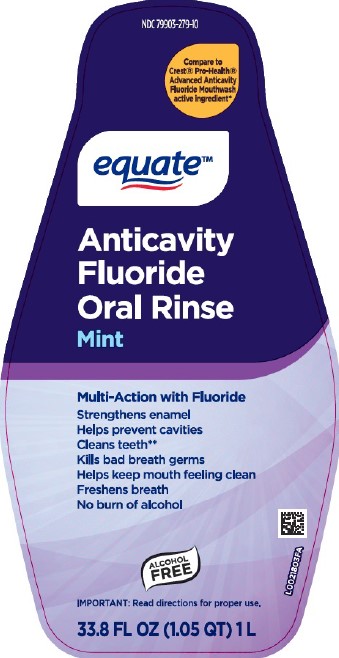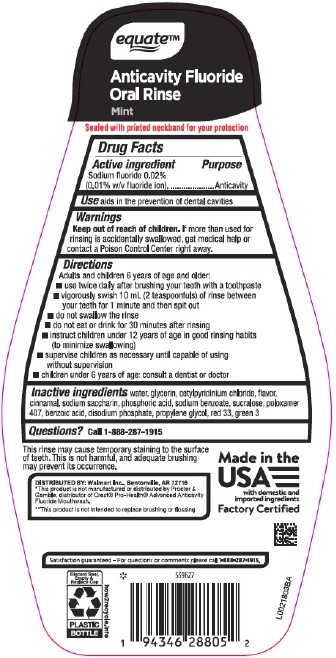 DRUG LABEL: Alcohol-Free Anticavity
NDC: 79903-279 | Form: LIQUID
Manufacturer: Walmart Inc.
Category: otc | Type: HUMAN OTC DRUG LABEL
Date: 20260227

ACTIVE INGREDIENTS: SODIUM FLUORIDE 0.1 mg/1 mL
INACTIVE INGREDIENTS: WATER; GLYCERIN; CETYLPYRIDINIUM CHLORIDE; CINNAMALDEHYDE; SACCHARIN SODIUM; PHOSPHORIC ACID; SODIUM BENZOATE; SUCRALOSE; POLOXAMER 407; BENZOIC ACID; SODIUM PHOSPHATE, DIBASIC, ANHYDROUS; PROPYLENE GLYCOL; D&C RED NO. 33; FD&C GREEN NO. 3

Equate 482.002/482AC
Alcohol Free Fluoride Violet Mint Mouthwash

Claims

equate ™

Anticavity Fluoride

Oral Rinse

Mint

Tamper Evident Statement

Sealed with printed neckband for your protection

Active ingredient

Sodium fluoride 0.02% (0.01% w/v fluoride ion)

Purpose

Anticavity

Use

aids in the prevention of dental cavities

Warnings

for this product

Keep out of reach of children.

If more than used for rinsing is accidentally swallowed, get medical help or contact a Poison Control Center right away.

Directions

Adults and children 6 years of age and older:

- use twice daily after brushing your teeth with a toothpaste
- vigorously swish 10 mL (2 teaspoonfuls) of rinse between your teeth for 1 minute and then spit out
- do not swallow the rinse
- do not eat or drink for 30 minutes after rinsing
- instruct children under 12 years of age in good rinsing habits (to minimize swallowing)
- supervise children as necessary until capable of using without supervision
- children under 6 years of age: consult a dentist or doctor

Inactive ingredients

water, glycerin, cetylpyridinium chloride, flavor, cinnamal, sodium saccharin, phosphoric acid, sodium benzoate, sucralose, poloxamer 407, benzoic acid, disodium phosphate, propylene glycol, red 33, green 3

Questions?

Call 1-888-287-1915

Disclaimers

This rinse may cause temporary staining to the surface of teeth. This is not harmful, and adequate brushing may prevent its occurence.

*This product is not manufactured or distributed by Procter & Gamble, distributor of Crest®Pro-Health®Advanced Anticavity Fluoride Mouthwash.

**This product is not intended to replace brushing or flossing.

Adverse reaction

DISTRIBUTED BY: Walmart Inc., Bentonville, AR 72716

Made in the USA with domestic and imported ingredients

Factory Certified

Satisfaction guaranteed - For questions or comments please call 1-888-287-1915.

Discard Seal, Empty & Replace Cap

PLASTIC BOTTLE

how2recycle.info

Principal display panel

NDC 79903-279-10

Compare to Crest®Pro-Health®Advanced Anticavity Fluoride Mouthwash active ingredient*

equate ™

Anticavity

Fluoride

Oral Rinse

Mint

Multi-Action with Fluoride

Strengthens enamel

Helps prevent cavities

Cleans teeth**

Kills bad breath germs

Helps keep mouth feeling clean

Freshens breath

No burn of alcohol

ALCOHOL FREE

IMPORTANT: Read directions for proper use.

33.8 FL OZ (1.05 QT) 1 L